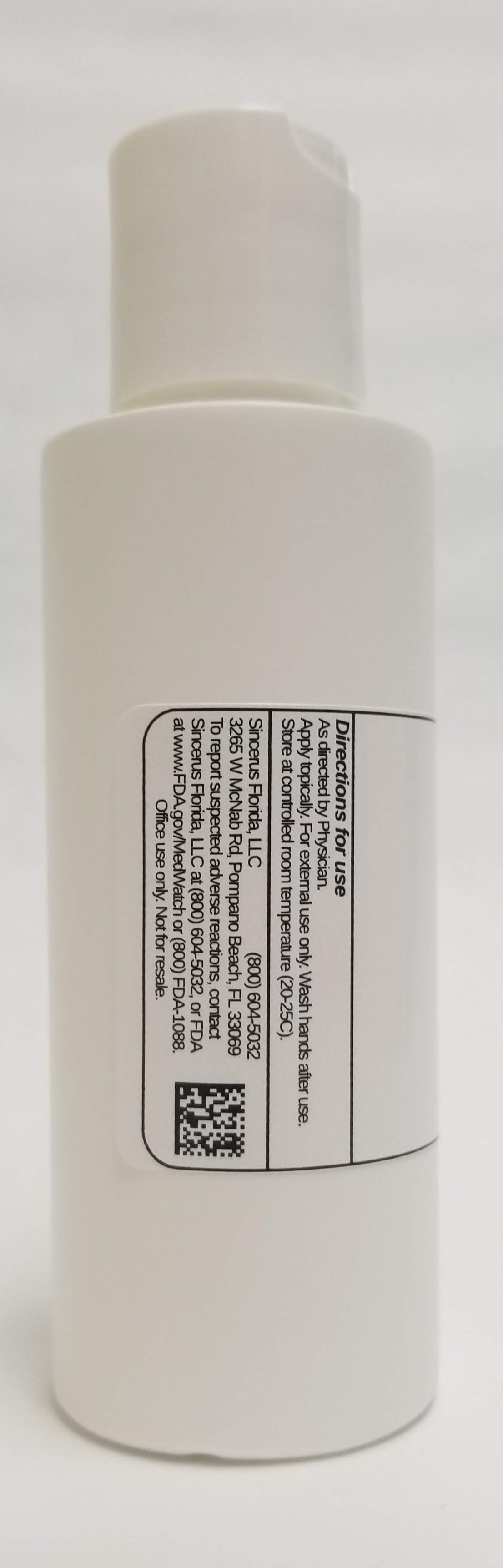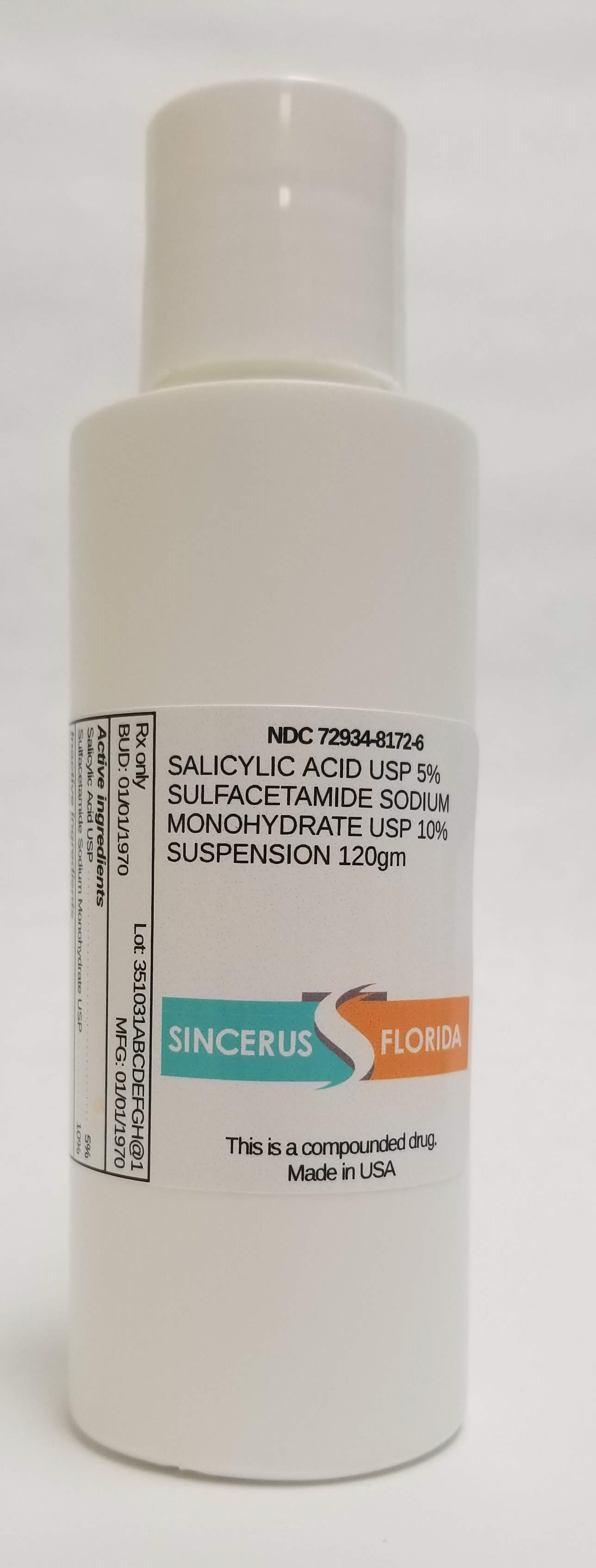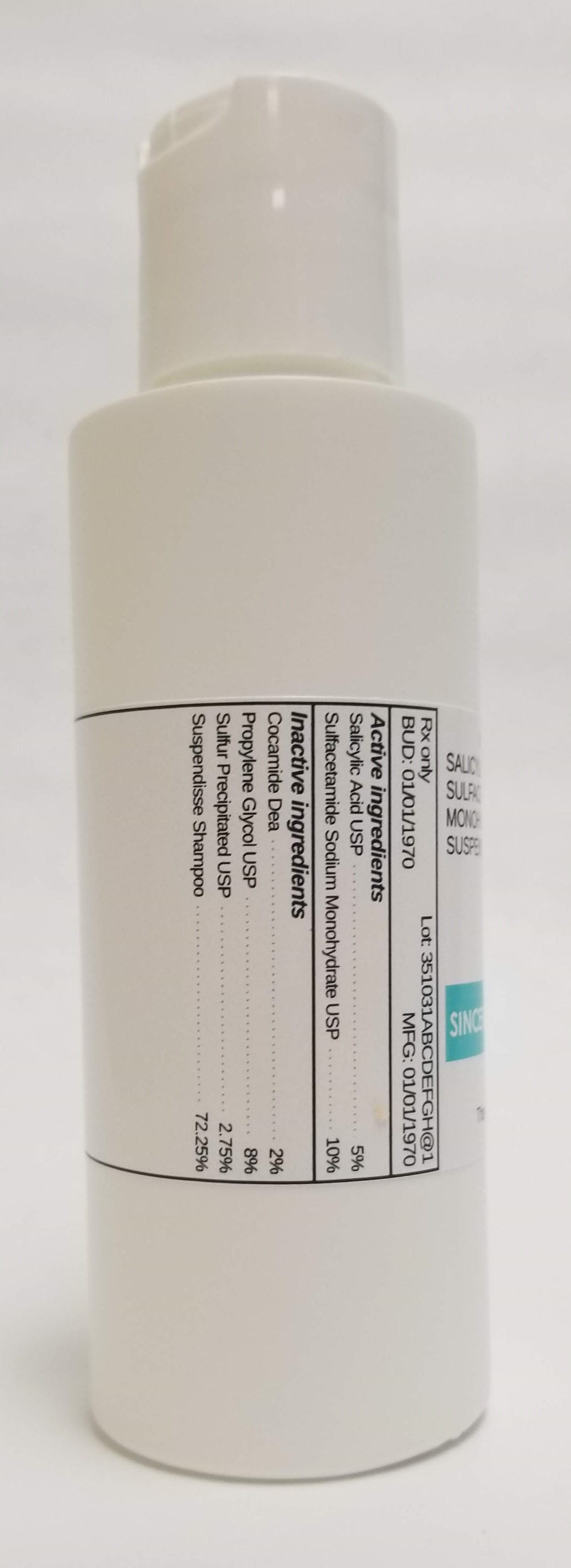 DRUG LABEL: SALICYLIC ACID 5% / SODIUM SULFACETAMIDE MONOHYDRATE 10%
NDC: 72934-8172 | Form: SUSPENSION
Manufacturer: Sincerus Florida, LLC
Category: prescription | Type: HUMAN PRESCRIPTION DRUG LABEL
Date: 20190516

ACTIVE INGREDIENTS: SALICYLIC ACID 5 g/100 g; SULFACETAMIDE SODIUM 10 g/100 g

SALICYLIC ACID 5% / SODIUM SULFACETAMIDE MONOHYDRATE 10%